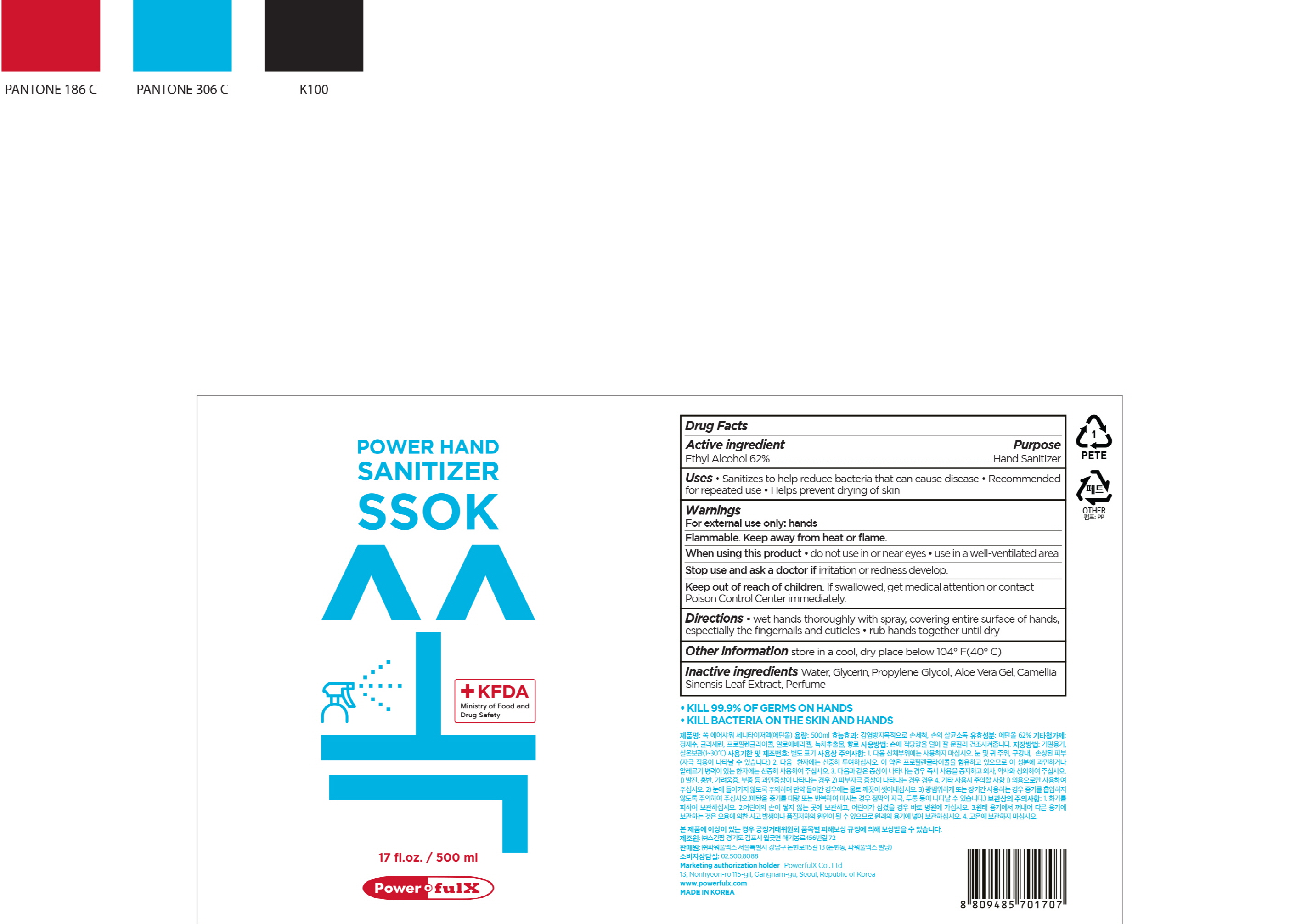 DRUG LABEL: PowerfulX SSOK Air Shower Sanitizer
NDC: 70042-0015 | Form: LIQUID
Manufacturer: POWERFULX CO.,LTD
Category: otc | Type: HUMAN OTC DRUG LABEL
Date: 20200529

ACTIVE INGREDIENTS: ALCOHOL 415 mL/500 mL
INACTIVE INGREDIENTS: PROPYLENE GLYCOL; WATER; ALOE VERA LEAF; GLYCERIN

Drug Facts

ACTIVE INGREDIENT

Alcohol

INACTIVE INGREDIENT

Water, Glycerin, Propylene Glycol, Aloe Vera Gel, Camellia Sinensis Leaf Extract, Perfume

PURPOSE

Antiseptic

KEEP OUT OF REACH OF THE CHILDREN

INDICATIONS AND USAGE

For the external use only

Do not use on the following body parts.
Around the eyes and ears, in the oral cavity, a wide range of body parts and damaged skin (may have irritating effects)
If the following symptoms appear, stop using them immediately and consult a doctor or pharmacist.

Symptoms of skin irritation

Other precautions

For external use only
Be careful not to get into your eyes, and if so, rinse well with clean water and consult a doctor or pharmacist.
Be careful not to inhale vapor when using it extensively or for a long time. (If you drink ethanol vapor in large quantities or repeatedly, irritation to the mucous membrane, headache, etc. may occur).
When repeated use on the same site, be careful as the skin may become rough due to degreasing.
When used in sealed bandages, cast bandages, packs, etc., irritation symptoms may appear.
Do not use for any other purpose.

DOSAGE AND ADMINISTRATION

Wet hands thoroughly with spray, covering entire surface of hands, especially the fingernails and cuticles

rub hands together until dry